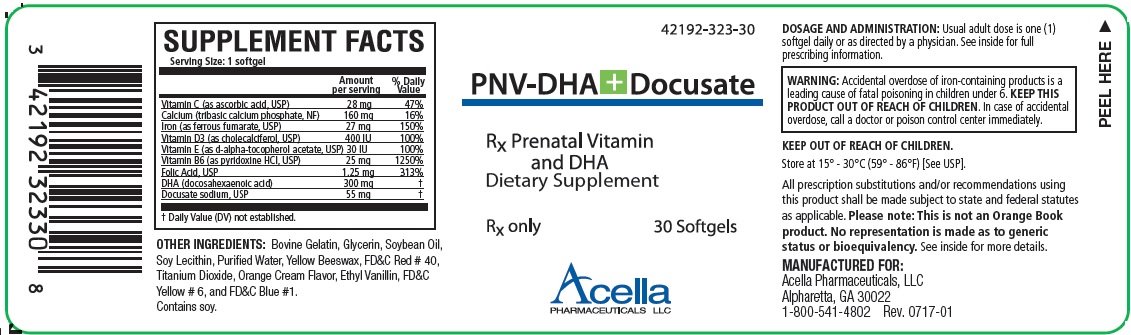 DRUG LABEL: PNV-DHA
NDC: 42192-323 | Form: CAPSULE, GELATIN COATED
Manufacturer: Acella Pharmaceuticals, LLC
Category: prescription | Type: HUMAN PRESCRIPTION DRUG LABEL
Date: 20240115

ACTIVE INGREDIENTS: ASCORBIC ACID 28 mg/1 1; CALCIUM 160 mg/1 1; FERROUS FUMARATE 27 mg/1 1; CHOLECALCIFEROL 400 [iU]/1 1; .ALPHA.-TOCOPHEROL ACETATE, DL- 30 [iU]/1 1; PYRIDOXINE 25 mg/1 1; FOLIC ACID 1.25 mg/1 1; DOCONEXENT 300 mg/1 1
INACTIVE INGREDIENTS: GELATIN TYPE B BOVINE (230 BLOOM); GLYCERIN; SOYBEAN OIL; LECITHIN, SOYBEAN; WATER; YELLOW WAX; FD&C RED NO. 40; TITANIUM DIOXIDE; ORANGE; ETHYL VANILLIN; FD&C YELLOW NO. 6; FD&C BLUE NO. 1

PNV-DHA + DOCUSATE

Rx Only

DESCRIPTION

PNV-DHA + Docusate is a prescription prenatal/postnatal multivitamin/multimineral softgel with DHA. Each softgel is red in color and imprinted with “323” on one side.

SUPPLEMENT FACTS
Serving Size: 1 softgel
 |  | Amount Per Serving | % Daily Value
Vitamin C (as ascorbic acid, USP) |  | 28 mg | 47%
Calcium (tribasic calcium phosphate, NF) |  | 160 mg | 16%
Iron (as ferrous fumarate, USP) |  | 27 mg | 150%
Vitamin D3 (as cholecalciferol, USP) |  | 400 IU | 100%
Vitamin E (as d-alpha-tocopherol acetate, USP) |  | 30 IU | 100%
Vitamin B6 (as pyridoxine HCl, USP) |  | 25 mg | 1250%
Folic Acid, USP |  | 1.25 mg | 313%
DHA (docosahexaenoic acid) |  | 300 mg | †
Docusate sodium, USP |  | 55 mg | †
† Daily Value (DV) not established.

OTHER INGREDIENTS

Bovine Gelatin, Glycerin, Soybean Oil, Soy Lecithin, Purified Water, Yellow Beeswax, FD&C Red # 40, Titanium Dioxide, Orange Cream Flavor, Ethyl Vanillin, FD&C Yellow # 6, and FD&C Blue #1. Contains soy.

INDICATIONS

PNV-DHA + Docusate is a multivitamin/mineral prescription dietary supplement indicated for use in improving the nutritional status of women prior to conception, throughout pregnancy, and in the postnatal period for both lactating and nonlactating mothers.

CONTRAINDICATIONS

This product is contraindicated in patients with a known hypersensitivity to any of the ingredients.

WARNING

Ingestion of more than 3 grams of omega-3 fatty acids (such as DHA) per day has been shown to have potential antithrombotic effects, including an increased bleeding time and International Normalized Ratio (INR). Administration of omega-3 fatty acids should be avoided in patients taking anticoagulants and in those known to have an inherited or acquired predisposition to bleeding.

BOXED WARNING

WARNING: Accidental overdose of iron-containing products is a leading cause of fatal poisoning in children under 6. KEEP THIS PRODUCT OUT OF REACH OF CHILDREN. In case of accidental overdose, call a doctor or poison control center immediately.

PRECAUTIONS

Folic acid alone is improper therapy in the treatment of pernicious anemia and other megaloblastic anemias where vitamin B12 is deficient. Folic acid in doses above 1.0 mg daily may obscure pernicious anemia in that hematologic remission can occur while neurological manifestations progress.

ADVERSE REACTIONS

Allergic sensitization has been reported following both oral and parenteral administration of folic acid.

CAUTION: Exercise caution to ensure that the prescribed dosage of DHA does not exceed 1 grams (1000 mg) daily.

DOSAGE AND ADMINISTRATION

Usual adult dose is one (1) softgel daily or as directed by a physician.

KEEP OUT OF REACH OF CHILDREN.

HOW SUPPLIED

PNV-DHA + Docusate is supplied in child-resistant bottles of 30 softgels (42192-323-30). The listed product number is not a National Drug Code, but has merely been formatted to comply with standard industry practice for pharmacy and insurance computer systems.

Store at 20°- 25°C (68° - 77°F); excursions permitted to 15°- 30°C (59° - 86°F) [See USP, “Controlled Room Temperature”]. Protect from light and heat.

KEEP THIS AND ALL MEDICATIONS OUT OF THE REACH OF CHILDREN.

All prescription substitutions and/or recommendations using this product shall be made subject to state and federal statutes as applicable. Please note: This is not an Orange Book product and has not been subjected to FDA therapeutic equivalency or other equivalency testing. No representation is made as to generic status or bioequivalency. Each person recommending a prescription substitution using this product shall make such recommendations based on each such person’s professional opinion and knowledge, upon evaluating the dietary ingredients, other ingredients and information provided herein.

THESE STATEMENTS HAVE NOT BEEN EVALUATED BY THE FOOD AND DRUG ADMINISTRATION. THIS PRODUCT IS NOT INTENDED TO DIAGNOSE, TREAT, CURE OR PREVENT ANY DISEASE.

MANUFACTURED FOR:
Acella Pharmaceuticals, LLC
Alpharetta, GA 30022
1-800-541-4802
Rev. 0717-01

PRINCIPAL DISPLAY PANEL - 30 Softgel Tablets

42192-323-30

PNV-DHA+Docusate

Rx Prenatal Vitamin and DHA
Dietary Supplement

Rx Only 30 Softgels

Acella
PHARMACEUTICALS, LLC